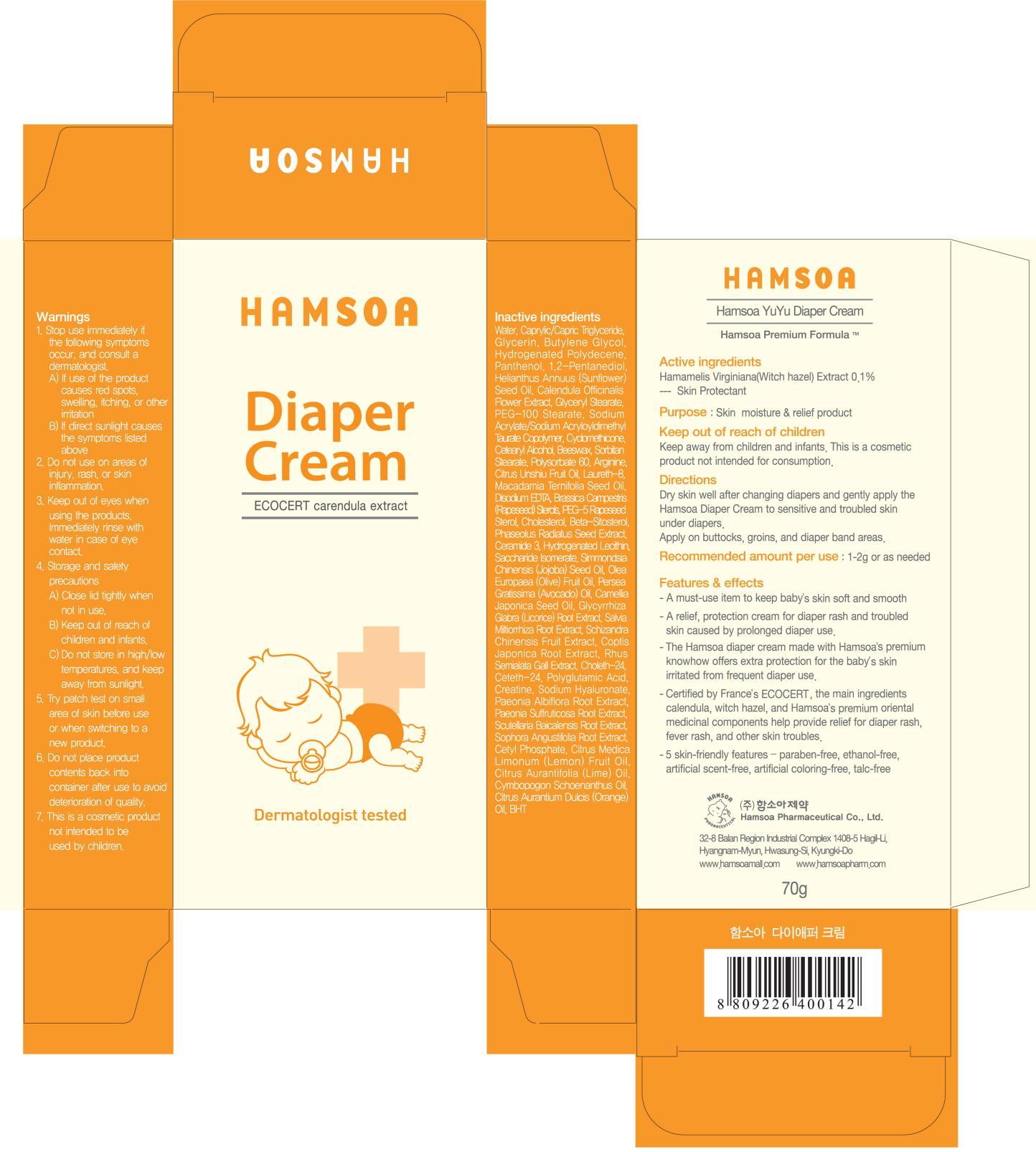 DRUG LABEL: HAMSOA YUYU DIAPER
NDC: 50964-010 | Form: CREAM
Manufacturer: HAMSOA PHARMACEUTICAL CO., LTD.
Category: otc | Type: HUMAN OTC DRUG LABEL
Date: 20120816

ACTIVE INGREDIENTS: WITCH HAZEL 0.07 g/70 g
INACTIVE INGREDIENTS: WATER; MEDIUM-CHAIN TRIGLYCERIDES; GLYCERIN; BUTYLENE GLYCOL; PANTHENOL; PENTYLENE GLYCOL; SUNFLOWER OIL; CALENDULA OFFICINALIS FLOWER

Active ingredient

Active ingredient: Witch hazel(Hamamelis Virginiana) 0.1%

Inactive ingredient

Inactive ingredients:
Water, Caprylic/Capric Triglyceride, Glycerin, Butylene Glycol, Hydrogenated Polydecene, Panthenol, 1,2-Pentanediol, Helianthus Annuus (Sunflower) Seed Oil, Calendula Officinalis Flower Extract, Glyceryl Stearate, PEG-100 Stearate, Sodium Acrylate/Sodium Acryloyldimethyl Taurate Copolymer, Cyclomethicone, Cetearyl Alcohol, Beeswax, Sorbitan Stearate, Polysorbate 60, Arginine, Citrus Unshiu Fruit Oil, Laureth-8, Macadamia Ternifolia Seed Oil, Disodium EDTA, Brassica Campestris (Rapeseed) Sterols, PEG-5 Rapeseed Sterol, Cholesterol, Beta-Sitosterol, Phaseolus Radiatus Seed Extract, Ceramide 3, Hydrogenated Lecithin, Saccharide Isomerate, Simmondsia Chinensis (Jojoba) Seed Oil, Olea Europaea (Olive) Fruit Oil, Persea Gratissima (Avocado) Oil, Camellia Japonica Seed Oil, Glycyrrhiza Glabra (Licorice) Root Extract, Salvia Miltiorrhiza Root Extract, Schizandra Chinensis Fruit Extract, Coptis Japonica Root Extract, Rhus Semialata Gall Extract, Choleth-24, Ceteth-24, Polyglutamic Acid, Creatine, Sodium Hyaluronate, Paeonia Albiflora Root Extract, Paeonia Suffruticosa Root Extract, Scutellaria Baicalensis Root Extract, Sophora Angustifolia Root Extract, Cetyl Phosphate, Citrus Medica Limonum (Lemon) Fruit Oil, Citrus Aurantifolia (Lime) Oil, Cymbopogon Schoenanthus Oil, Citrus Aurantium Dulcis (Orange) Oil, BHT

PURPOSE

Purpose: Skin moisture and relief product

Warnings

1. Stop use immediately if the following symptoms occur, and consult a dermatologist.
A) If use of the product causes red spots, swelling, itching, or other irritation
B) If direct sunlight causes the symptoms listed above
2. Do not use on areas of injury, rash, or skin inflammation.
3. Keep out of eyes when using the products. Immediately rinse with water in case of eye contact.
4. Storage and safety precautions
A) Close lid tightly when not in use.
B) Keep out of reach of children and infants.
C)Do not store in high/low temperatures, and keep away from sunlight.
5. Try patch test on small area of skin before use or when switching to a new product.
6. Do not place product contents back into container after use to avoid deterioration of quality.
7. This is a cosmetic product not intended to be used by children

Keep out of reach of children

Keep away from children and infants.
This is a cosmetic product not intended for consumption.

INDICATIONS AND USAGE

Directions:
Dry skin well after changing diapers and gently apply the Hamsoa Diaper Cream to sensitive and troubled skin under diapers.
Apply on buttocks, groins, and diaper band areas.

DOSAGE AND ADMINISTRATION

Recommended amount per use: 1-2g or as needed